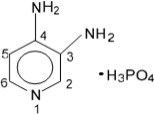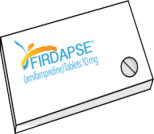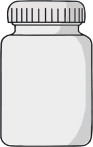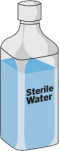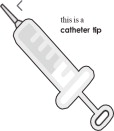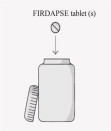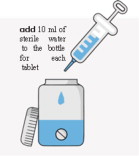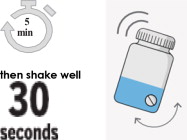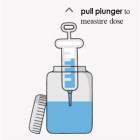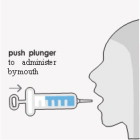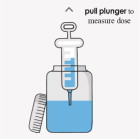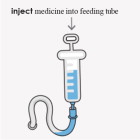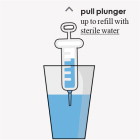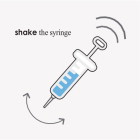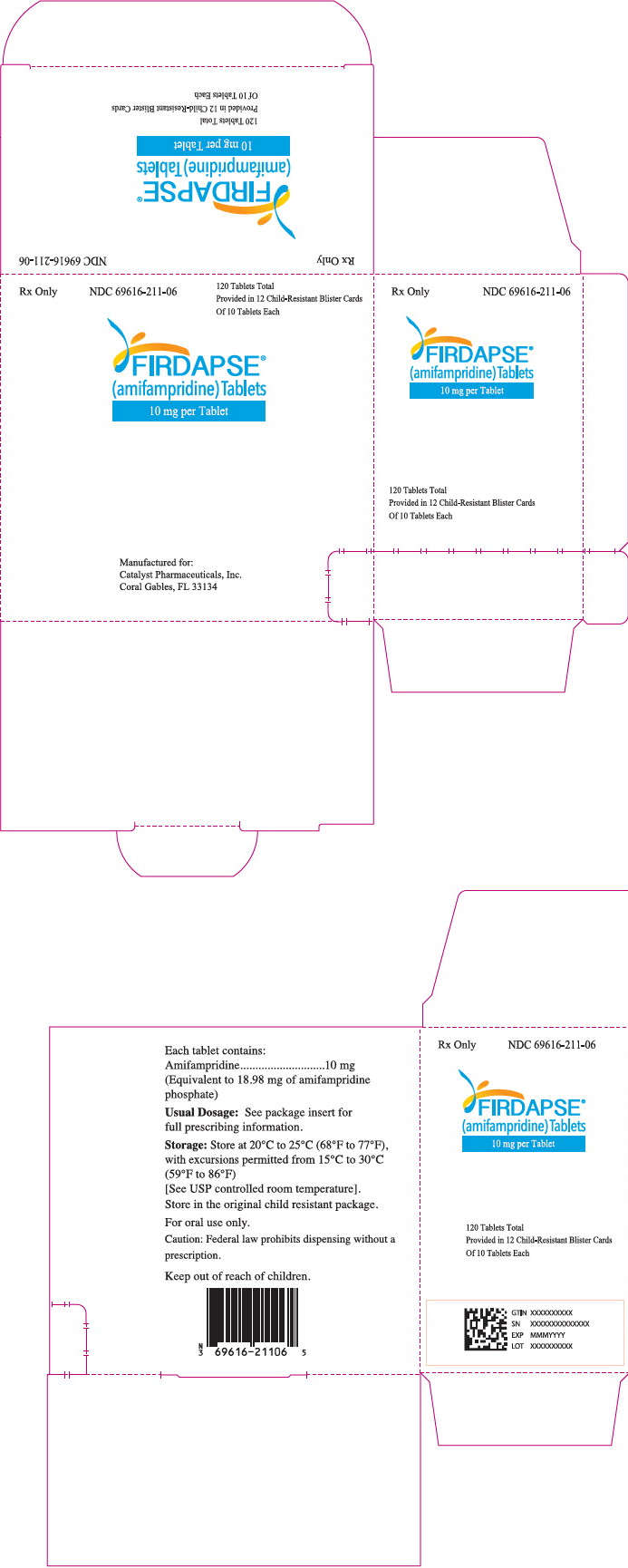 DRUG LABEL: Firdapse

NDC: 69616-211 | Form: TABLET
Manufacturer: Catalyst Pharmaceuticals, Inc.

Category: prescription | Type: HUMAN PRESCRIPTION DRUG LABEL
Date: 20240531

ACTIVE INGREDIENTS: amifampridine phosphate
 10 mg/1 1
INACTIVE INGREDIENTS: microcrystalline cellulose; SILICON DIOXIDE; calcium stearate

HIGHLIGHTS OF PRESCRIBING INFORMATION

These highlights do not include all the information needed to use FIRDAPSE® safely and effectively. See full prescribing information for FIRDAPSE®.
FIRDAPSE® (amifampridine) tablets, for oral use
Initial U.S. Approval: 2018

RECENT MAJOR CHANGES

Dosage and Administration (2.1) | 5/2024

1 INDICATIONS AND USAGE

FIRDAPSE is a potassium channel blocker indicated for the treatment of Lambert-Eaton myasthenic syndrome (LEMS) in adults and pediatric patients 6 years of age and older. (1)

2 DOSAGE AND ADMINISTRATION

- Administer orally in divided doses (3 to 5 times daily). (2.1)
- The recommended starting dosage for adults (any weight) and pediatric patients weighing 45 kg or more is 15 mg to 30 mg daily, in divided doses. (2.1)
  - Dosage can be increased by 5 mg daily every 3 to 4 days. (2.1)
  - The maximum single dose is 20 mg. (2.1)
  - Dosage is not to exceed a maximum of 100 mg daily. (2.1)
- The recommended starting dosage for pediatric patients weighing less than 45 kg is 5 mg to 15 mg daily, in divided doses. (2.1)
  - Dosage can be increased by 2.5 mg daily every 3 to 4 days. (2.1)
  - The maximum single dose is 10 mg. (2.1)
  - Dosage is not to exceed a maximum of 50 mg daily. (2.1)
- The recommended starting dosage for adult and pediatric patients with renal impairment, hepatic impairment, and in known N-acetyltransferase 2 (NAT2) poor metabolizers is the lowest recommended initial daily dosage (2.1, 2.2, 2.3, 2.4)
- For patients with a dosage adjustment of less than 5 mg increments, or who have difficulty swallowing, or require feeding tube, a l mg/mL suspension can be prepared. (2.5)

3 DOSAGE FORMS AND STRENGTHS

- Tablets: 10 mg, functionally scored. (3)

4 CONTRAINDICATIONS

FIRDAPSE is contraindicated in patients with:

- A history of seizures (4)
- Hypersensitivity to amifampridine or another aminopyridine (4)

5 WARNINGS AND PRECAUTIONS

- Seizures: FIRDAPSE can cause seizures. Consider discontinuation or dose-reduction of FIRDAPSE in patients who have a seizure while on treatment. (5.1)
- Hypersensitivity reactions: If a hypersensitivity reaction such as anaphylaxis occurs, FIRDAPSE should be discontinued and appropriate therapy initiated. (5.2)

6 ADVERSE REACTIONS

The most common (> 10%) adverse reactions are: paresthesia, upper respiratory tract infection, abdominal pain, nausea, diarrhea, headache, elevated liver enzymes, back pain, hypertension, and muscle spasms. (6)

To report SUSPECTED ADVERSE REACTIONS, contact Catalyst Pharmaceuticals at 1-844-347-3277 (1-844-FIRDAPSE) or FDA at 1-800-FDA-1088 or www.fda.gov/medwatch.

7 DRUG INTERACTIONS

- Drugs that lower seizure threshold: Concomitant use may lead to an increased risk of seizures. (7.1)
- Drugs with cholinergic effects (e.g., direct or indirect cholinesterase inhibitors): Concomitant use may increase the cholinergic effects of FIRDAPSE and of those drugs and increase the risk of adverse reactions. (7.2)

8 USE IN SPECIFIC POPULATIONS

- Pregnancy: Based on animal data, may cause fetal harm. (8.1)

FULL PRESCRIBING INFORMATION

1 INDICATIONS AND USAGE

FIRDAPSE® is indicated for the treatment of Lambert-Eaton myasthenic syndrome (LEMS) in adults and pediatric patients 6 years of age and older.

2 DOSAGE AND ADMINISTRATION

2.1 Dosage Information

The recommended oral dosage of FIRDAPSE for adults and pediatric patients 6 years of age and older is included in Table 1. For pediatric patients, the recommended dosing regimen is dependent on body weight. Dosage should be increased every 3 to 4 days based on clinical response and tolerability. Titration increments should not exceed those shown in Table 1.

Table 1: Recommended Oral Dosage for the Treatment of LEMS in Adults and Pediatric Patients 6 Years of Age and Older
Age and Body Weight | Initial Daily Dosage* | Titration Regimen | Maximum Single Dose | Maximum Total Daily Maintenance Dosage
- Adults (any weight) - Pediatric patients weighing 45 kg or more | 15 mg to 30 mg daily, in 3 to 5 divided doses | Increase total daily dosage by 5 mg every 3 or 4 days | 20 mg | 100 mg Given in divided doses
- Pediatric patients weighing less than 45 kg | 5 mg to 15 mg daily, in 3 to 5 divided doses | Increase total daily dosage by 2.5 mg every 3 or 4 days | 10 mg | 50 mg Given in divided doses
*See Dosage and Administration (2.5) for a method to achieve these doses

Missed Dose

If a dose is missed, patients should not take double or extra doses.

2.2 Patients with Renal Impairment

The recommended starting dosage of FIRDAPSE in patients with renal impairment [creatinine clearance (CLcr) 15 to 90 mL/min] is the lowest recommended initial daily dosage (i.e., 15 mg daily for pediatric patients weighing 45 kg or more and for adults, and 5 mg daily for pediatric patients weighing less than 45 kg) taken orally in divided doses. No dosage recommendation for FIRDAPSE can be made for patients with end-stage renal disease [see Dosage and Administration (2.1), Use in Specific Populations (8.6), and Clinical Pharmacology (12.3)].

2.3 Patients with Hepatic Impairment

The recommended starting dosage of FIRDAPSE in patients with any degree of hepatic impairment is the lowest recommended initial daily dosage (i.e., 15 mg daily for pediatric patients weighing 45 kg or more and for adults, and 5 mg daily for pediatric patients weighting less than 45 kg) taken orally in divided doses [see Dosage and Administration (2.1), Use in Specific Populations (8.7), and Clinical Pharmacology (12.3)].

2.4 Known N-acetyltransferase 2 (NAT2) Poor Metabolizers

The recommended starting dosage of FIRDAPSE in known N-acetyltransferase 2 (NAT2) poor metabolizers is the lowest recommended initial daily dosage (i.e., 15 mg daily for pediatric patients weighing 45 kg or more and for adults, and 5 mg daily for pediatric patients weighing less than 45 kg) taken orally in divided doses [see Dosage and Administration (2.1), Use in Specific Populations (8.8), and Clinical Pharmacology (12.5)].

2.5 Administration Instructions

FIRDAPSE can be taken without regard to food.

Preparation of a 1mg/mL Suspension (see the Instructions for Use for full instructions on how to prepare the 1mg/mL suspension)

When patients require a dosage in less than 5 mg increments, have difficulty swallowing tablets, or require feeding tubes, a 1 mg/mL suspension can be prepared (e.g., by placing the required number of tablets in a 50 to 100 mL container, adding 10 mL of sterile water for each tablet, waiting for 5 minutes, and shaking well for 30 seconds).

Crushing the tablets prior to making the suspension is not necessary. After preparation of the suspension, an oral syringe can be used to draw up and administer the correct dose by mouth or by feeding tube.

Storage of 1mg/mL Prepared Suspension

Refrigerate the suspension between doses and shake well before drawing up each dose. The suspension can be stored under refrigeration [between 2°C and 8°C (36°F and 46°F)] for up to 24 hours. Discard any unused portion of the suspension after 24 hours.

3 DOSAGE FORMS AND STRENGTHS

FIRDAPSE tablets contain 10 mg amifampridine and are white to off-white, round, and functionally scored. Each tablet is debossed on the non-scored side with “CATALYST” and on the scored side with “211” above the score and “10” below the score.

4 CONTRAINDICATIONS

FIRDAPSE is contraindicated in patients with:

- A history of seizures [see Warnings and Precautions (5.1)]
- Hypersensitivity to amifampridine phosphate or another aminopyridine [see Warnings and Precautions (5.2)]

5 WARNINGS AND PRECAUTIONS

5.1 Seizures

FIRDAPSE can cause seizures. Seizures have been observed in patients without a history of seizures taking FIRDAPSE at the recommended doses, at various times after initiation of treatment, at an incidence of approximately 2%. Many of the patients were taking medications or had comorbid medical conditions that may have lowered the seizure threshold [see Drug Interactions (7.1)]. Seizures may be dose-dependent. Consider discontinuation or dose-reduction of FIRDAPSE in patients who have a seizure while on treatment. FIRDAPSE is contraindicated in patients with a history of seizures.

5.2 Hypersensitivity

In clinical trials, hypersensitivity reactions and anaphylaxis associated with FIRDAPSE administration have not been reported. Anaphylaxis has been reported in patients taking another aminopyridine; therefore, it may occur with FIRDAPSE. If anaphylaxis occurs, administration of FIRDAPSE should be discontinued and appropriate therapy initiated.

6 ADVERSE REACTIONS

The following serious adverse reactions are described elsewhere in the labeling:

- Seizures [see Warnings and Precautions (5.1)]
- Hypersensitivity [see Warnings and Precautions (5.2)]

6.1 Clinical Trials Experience

Adults

Because clinical trials are conducted under widely varying conditions, adverse reaction rates observed in the clinical trials of a drug cannot be directly compared to rates in the clinical trials of another drug and may not reflect the rates observed in practice.

In controlled and uncontrolled clinical trials (Study 1 and 2) in patients with LEMS [see Clinical Studies (14)], 63 patients were treated with FIRDAPSE, including 40 patients treated for more than 6 months, and 39 patients treated for more than 12 months. In an expanded access program, 139 patients with LEMS were treated with FIRDAPSE, including 102 patients treated for more than 6 months, 77 patients treated for more than 12 months, and 53 patients treated for more than 18 months. In the expanded access program, patients were treated with FIRDAPSE with up to 100 mg daily in divided doses.

Study 1 was a double-blind, placebo-controlled, randomized discontinuation study in adults with LEMS. Following an initial open- label run-in phase (up to 90 days), patients were randomized to either continue FIRDAPSE treatment or transition to placebo, for a 14-day double-blind phase. Following final assessments, patients were allowed to resume FIRDAPSE treatment for up to 2 years (open-label long-term safety phase of the study).

During the open-label run-in phase of Study 1, 53 patients received FIRDAPSE for an average of 81 days at a mean daily dosage of 50.5 mg/day. The mean patient age was 52.1 years and 66% were female. There were 42 patients who had no prior exposure to FIRDAPSE at the initiation of this study. Table 2 shows adverse reactions with an incidence of 5% or greater occurring in the 42 LEMS patients newly initiated on treatment with FIRDAPSE during the run-in phase of the study.

Table 2. Adverse Reactions in ≥5% of LEMS Patients Newly Treated with FIRDAPSE in Study 1
Adverse Reaction | FIRDAPSE N=42 %
Paresthesia* | 62
Upper respiratory tract infection | 33
Abdominal pain | 14
Nausea | 14
Diarrhea | 14
Headache | 14
Elevated liver enzymes** | 14
Back pain | 14
Hypertension | 12
Muscle spasms | 12
Dizziness | 10
Asthenia | 10
Muscular weakness | 10
Pain in extremity | 10
Cataract | 10
Constipation | 7
Bronchitis | 7
Fall | 7
Lymphadenopathy | 7
*Includes paresthesia, oral paresthesia, oral hypoesthesia
**Includes elevated alanine aminotransferase (ALT), aspartate aminotransferase (AST), lactate dehydrogenase (LDH), and gamma-glutamyl transferase (GGT)

Other Adverse Reactions

In the overall population treated in Study 1 (n=53), including the double-blind phase and the 2-year open-label long-term safety phase, additional adverse reactions occurring in at least 5% of the patients included: dyspnea, urinary tract infection, gastroesophageal reflux, insomnia, peripheral edema, pyrexia, viral infection, blood creatine phosphokinase increase, depression, erythema, hypercholesterolemia, and influenza. These patients received a mean daily dosage of 66 mg of FIRDAPSE.

Pediatrics

Safety of FIRDAPSE was evaluated in pediatric patients in an expanded access program, where 21 pediatric patients received FIRDAPSE for at least 1 year. Adverse reactions reported in pediatric patients were similar to those seen in adult patients, with the exception of clinically significant weight loss in two pediatric patients at doses of 60 mg per day and higher.

7 DRUG INTERACTIONS

7.1 Drugs that Lower Seizure Threshold

The concomitant use of FIRDAPSE and drugs that lower seizure threshold may lead to an increased risk of seizures [see Warnings and Precautions (5.1)]. The decision to administer FIRDAPSE concomitantly with drugs that lower the seizure threshold should be carefully considered in light of the severity of the associated risks.

7.2 Drugs with Cholinergic Effects

The concomitant use of FIRDAPSE and drugs with cholinergic effects (e.g., direct or indirect cholinesterase inhibitors) may increase the cholinergic effects of FIRDAPSE and of those drugs and increase the risk of adverse reactions.

8 USE IN SPECIFIC POPULATIONS

8.1 Pregnancy

Pregnancy Exposure Registry

There is a pregnancy exposure registry that monitors pregnancy outcomes in women exposed to FIRDAPSE during pregnancy. Physicians are encouraged to enroll pregnant patients, or pregnant women may register themselves in the registry by calling 855- 212-5856 (toll-free), using the Fax number 877-867-1874 (toll-free), by contacting the Pregnancy Coordinating Center at firdapsepregnancyregistry@ubc.com, or by visiting the study website www.firdapsepregnancystudy.com.

Risk Summary

There are no data on the developmental risk associated with the use of FIRDAPSE in pregnant women. In animal studies, administration of amifampridine phosphate to rats during pregnancy and lactation resulted in developmental toxicity (increase in stillbirths and pup deaths, reduced pup weight, and delayed sexual development) at doses associated with maternal plasma drug levels lower than therapeutic drug levels (see Animal Data). In the U.S. general population, the estimated background risk of major birth defects and miscarriage in clinically recognized pregnancies is 2-4% and 15-20%, respectively. The background risk of major birth defects and miscarriage for the indicated population is unknown.

Data

Animal Data

Oral administration of amifampridine phosphate (0, 7.5, 22.5, or 75 mg/kg/day) to female rats prior to and during mating and continuing throughout organogenesis produced no adverse effects on embryofetal development. The highest dose tested is approximately 4 times the maximum recommended human dose (MRHD) of amifampridine (100 mg/day) on a body surface area (mg/m^2) basis. Oral administration of amifampridine phosphate (0, 9, 30, or 57 mg/kg/day) to pregnant rabbits throughout organogenesis produced no adverse effects on embryofetal development. The highest dose tested is approximately 6 times the MRHD of amifampridine on a body surface area (mg/m^2) basis.

Oral administration of amifampridine phosphate (0, 7.5, 22.5, or 75 mg/kg/day) to female rats throughout pregnancy and lactation resulted in an increase in stillbirths and pup deaths, reduced pup weight, and delayed sexual development in female pups at the mid and high doses tested. The no-effect dose (7.5 mg/kg/day amifampridine phosphate) for adverse developmental effects is associated with a plasma amifampridine exposure (AUC) less than that in humans at the MRHD of amifampridine.

8.2 Lactation

Risk Summary

There are no data on the presence of FIRDAPSE in human milk, the effects on the breastfed infant, or the effects on milk production. The developmental and health benefits of breastfeeding should be considered along with the mother's clinical need for FIRDAPSE and any potential adverse effects on the breastfed infant from FIRDAPSE or from the underlying maternal condition.

In lactating rat, amifampridine was excreted in milk and reached levels similar to those in maternal plasma.

8.4 Pediatric Use

Safety and effectiveness of FIRDAPSE for the treatment of LEMS have been established in pediatric patients 6 years of age and older. Use of FIRDAPSE for this indication is supported by evidence from adequate and well-controlled studies of FIRDAPSE in adults with LEMS, pharmacokinetic data in adult patients, pharmacokinetic modeling and simulation to identify the dosing regimen in pediatric patients, and safety data from pediatric patients aged 6 years and older [see Adverse Reactions (6.1), Clinical Pharmacology (12.3), and Clinical Studies (14)].

Safety and effectiveness in pediatric patients below the age of 6 years have not been established.

8.5 Geriatric Use

Clinical studies of FIRDAPSE did not include a sufficient number of subjects aged 65 and over (19 of 63 patients in Studies 1 and 2) to determine whether they respond differently from younger subjects. Other reported clinical experience has not identified differences in responses between the elderly and younger patients. In general, dose selection for an elderly patient should be cautious, usually starting at the low end of the dosing range, reflecting the greater frequency of decreased hepatic, renal, or cardiac function, and of concomitant disease or other drug therapy [see Dosage and Administration (2.2, 2.3) and Drug Interactions (7.1, 7.2)].

8.6 Renal Impairment

Renal clearance is an elimination pathway for amifampridine and the inactive metabolite, 3-N-acetyl-amifampridine, and exposure of amifampridine is higher in subjects with renal impairment [see Clinical Pharmacology (12.3)]. Therefore, in patients with renal impairment, FIRDAPSE should be initiated at the lowest recommended initial daily dosage, and patients should be closely monitored for adverse reactions [see Dosage and Administration (2.2)]. Consider dosage modification or discontinuation of FIRDAPSE for patients with renal impairment as needed based on clinical effect and tolerability. The safety, efficacy, and pharmacokinetics of amifampridine have not been studied in patients with end-stage renal disease (CLcr <15 mL/min or patients requiring dialysis). No dosage recommendation for FIRDAPSE can be made for patients with end-stage renal disease.

8.7 Hepatic Impairment

In patients with any degree of hepatic impairment, FIRDAPSE should be initiated at the lowest recommended initial daily dosage, and patients should be monitored for adverse reactions [see Dosage and Administration (2.3)]. Consider dosage modification or discontinuation of FIRDAPSE for patients with hepatic impairment as needed based on clinical effect and tolerability.

8.8 NAT2 Poor Metabolizers

Exposure of FIRDAPSE is increased in patients who are N-acetyltransferase 2 (NAT2) poor metabolizers [see Clinical Pharmacology (12.5)]. Therefore, initiate FIRDAPSE in patients who are known NAT2 poor metabolizers at the lowest recommended initial daily dosage and monitor for adverse reactions [see Dosage and Administration (2.4)]. Consider dosage modification of FIRDAPSE for patients who are known NAT2 poor metabolizers as needed based on clinical effect and tolerability.

10 OVERDOSAGE

Overdose with FIRDAPSE was not reported during clinical studies.

In a case report, a 65-year-old patient with LEMS inadvertently received a total daily amifampridine dose of 360 mg/day (approximately 4 times the maximum recommended total daily dose) and was hospitalized for general weakness, paresthesia, nausea, vomiting, and palpitations. The patient developed convulsions and paroxysmal supraventricular tachycardia, and four days after admission, experienced cardiac arrest. The patient was resuscitated and ultimately recovered following withdrawal of amifampridine.

Patients with suspected overdose with FIRDAPSE should be monitored for signs or symptoms of exaggerated FIRDAPSE adverse reactions or effects, and appropriate symptomatic treatment instituted immediately.

11 DESCRIPTION

The active ingredient of FIRDAPSE is amifampridine phosphate, which is a voltage-gated potassium channel blocker. Amifampridine phosphate is described chemically as 3,4-diaminopyridine phosphate with a molecular weight of 207.1 and a molecular formula of C5H7N3 • H3PO4. The structural formula is:

Amifampridine phosphate is a white, crystalline powder that is freely soluble in water, and slightly soluble in solvents ethanol, methanol and acetic acid. A 1% aqueous solution of amifampridine phosphate has a pH of 4.4 at ambient conditions.

Each FIRDAPSE tablet contains 10 mg amifampridine (equivalent to 18.98 mg amifampridine phosphate). The tablet formulation includes the following inactive ingredients: calcium stearate, colloidal silicon dioxide, and microcrystalline cellulose.

FIRDAPSE tablets are intended for oral administration only.

12 CLINICAL PHARMACOLOGY

12.1 Mechanism of Action

The mechanism by which amifampridine exerts its therapeutic effect in LEMS patients has not been fully elucidated. Amifampridine is a broad-spectrum potassium channel blocker.

12.2 Pharmacodynamics

The effect of FIRDAPSE on QTc interval prolongation was studied in a double blind, randomized, placebo and positive controlled study in 52 healthy individuals who are slow acetylators. At an exposure 2-fold the expected maximum therapeutic exposure of amifampridine, FIRDAPSE did not prolong QTc to any clinically relevant extent.

12.3 Pharmacokinetics

The pharmacokinetics of amifampridine are similar between healthy individuals and LEMS patients. Following single and multiple doses, AUC, Cmax and Cmin were highly variable between individuals. FIRDAPSE exposure increased proportionally with dose across the range of 20 mg to 80 mg single oral doses.

Absorption

Amifampridine peak plasma concentration is reached 20 minutes to 1 hour after administration. Food does not have a clinically significant effect on the exposure of amifampridine.

Elimination

Amifampridine is eliminated primarily through metabolism to 3-N-acetyl-amifampridine and to a smaller extent through the kidneys. The terminal half-life ranges from 1.8 to 2.5 hours in healthy subjects.

Metabolism

Amifampridine is extensively metabolized by N-acetyltransferase 2 (NAT2) to 3-N-acetyl-amifampridine, which is considered an inactive metabolite.

Excretion

Following administration of FIRDAPSE to healthy subjects, 93% to 100% of the administered dose was eliminated in the urine as amifampridine or 3-N-acetyl amifampridine over 24 hours.

Specific Populations

Pediatric Patients (6 Years of Age and Older)

A population pharmacokinetic analysis showed that body weight significantly correlates with the clearance of amifampridine; clearance increased with an increase in body weight. A weight-based dosing regimen is necessary to achieve amifampridine exposures in pediatric patients 6 years of age and older, similar to the exposures observed in adults at recommended doses of FIRDAPSE [see Dosage and Administration (2.1) and Clinical Studies (14)].

Patients with Renal Impairment

Pharmacokinetic data are available from a study of 24 otherwise healthy subjects with impaired renal function who received a single 10-mg dose of FIRDAPSE. The exposure of amifampridine (measured as AUC) was 2- to 3-fold higher in subjects with moderate (CLcr 30-59 mL/min) or severe (CLcr 15-29 mL/min) renal impairment than in subjects with normal renal function (CLcr greater than or equal to 90 mL/min). Compared with subjects with normal renal function, subjects with mild renal impairment (CLcr 60-89 mL/min) had a 36% increase in exposure. Therefore, FIRDAPSE should be initiated at the lowest recommended initial daily dosage in patients with renal impairment, and such patients should be closely monitored for adverse reactions [see Dosage and Administration (2.2) and Use in Specific Populations (8.6)]. Cmax was marginally affected by renal impairment.

Patients with Hepatic Impairment

A study was conducted to determine the PK, safety, and tolerability of FIRDAPSE (amifampridine phosphate) administered at 10 mg to subjects with moderate hepatic impairment (N = 7) compared to demographically matched healthy subjects with normal hepatic function (N = 9). The subjects with moderate hepatic impairment had a 22% higher Cmax and a 33% higher AUCinf for amifampridine than subjects with normal hepatic function. FIRDAPSE was not evaluated in subjects with severe hepatic impairment [see Dosage and Administration (2.3) and Use in Specific Populations (8.7)].

12.5 Pharmacogenomics

Genetic variants in the N-acetyltransferase gene 2 (NAT2) affect the rate and extent of FIRDAPSE metabolism. Poor metabolizers, also referred to as “slow acetylators” (i.e., carriers of two reduced function alleles), have 3.5- to 4.5-fold higher Cmax, and 5.6- to 9- fold higher AUC than normal metabolizers, also referred to as “fast/rapid acetylators” (i.e., carriers of two normal function alleles). Therefore, FIRDAPSE should be initiated at the lowest recommended initial daily dosage in known NAT2 poor metabolizers, and such patients should be closely monitored for adverse reactions [see Dosage and Administration (2.4) and Use in Specific Populations (8.8)]. In the general population, the NAT2 poor metabolizer phenotype prevalence is 40–60% in the White and African American populations, and in 10–30% in Asian ethnic populations (individuals of Japanese, Chinese, or Korean descent).

13 NONCLINICAL TOXICOLOGY

13.1 Carcinogenesis, Mutagenesis, Impairment of Fertility

Carcinogenicity

In a 104-week carcinogenicity study in rats, oral administration of amifampridine phosphate (0, 15, 48, or 105 mg/kg/day) resulted in an increase in uterine tumors (endometrial carcinoma and combined endometrial adenoma/endometrial carcinoma/squamous cell carcinoma) at the mid and high doses tested. The low dose, not associated with an increase in tumors, is less than the maximum recommended human dose (MRHD) of amifampridine (100 mg/day) on a body surface area (mg/m^2 basis).

In a 26-week carcinogenicity study in transgenic (Tg.rasH2) mice, oral administration of amifampridine phosphate (0, 2, 7, or 21 mg/kg/day in males and 0, 3, 10, or 30 mg/kg/day in females) resulted in no increase in tumors.

Mutagenesis

Amifampridine phosphate was negative in the in vitro bacterial reverse mutation and in vivo rat micronucleus assays. Amifampridine phosphate was positive for clastogenicity in the in vitro mouse lymphoma tk assay in the absence of metabolic activation.

Impairment of Fertility

Oral administration of amifampridine phosphate (0, 7.5, 22.5, or 75 mg/kg/day) to male and female rats prior to and during mating, and continuing in females throughout organogenesis, produced no adverse effects on fertility. The highest dose tested is approximately 4 times the MRHD of amifampridine on a body surface area (mg/m^2) basis.

14 CLINICAL STUDIES

The efficacy of FIRDAPSE for the treatment of LEMS was demonstrated in two randomized, double-blind, placebo-controlled discontinuation studies. A total of 64 adults (age 21 to 88 years) with LEMS were enrolled (Study 1 and Study 2). The studies enrolled patients with a confirmed diagnosis of LEMS based on either neurophysiology studies or a positive anti-P/Q type voltage-gated calcium channel antibody test. Patients were required to be on an adequate and stable dosage (30 to 80 mg daily) of amifampridine phosphate prior to entering the randomized discontinuation phases of both studies.

The two co-primary measures of efficacy in both studies were the change from baseline to the end of the discontinuation period in the Quantitative Myasthenia Gravis (QMG) score and in the Subject Global Impression (SGI) score.

The QMG is a 13-item physician-rated categorical scale assessing muscle weakness. Each item is assessed on a 4-point scale, where a score of 0 represents no weakness, and a score of 3 represents severe weakness (total score 0-39). Higher scores represent greater impairment.

The SGI is a 7-point scale on which patients rated their global impression of the effects of the study treatment on their physical well- being. Lower scores on the SGI represent lower perceived benefit with the study treatment.

A key secondary efficacy endpoint was the clinical global impression improvement (CGI-I) score, a 7-point scale on which the treating physician rated the global impression of change in clinical symptoms. A higher CGI-I score indicates a perceived worsening of clinical symptoms.

Study 1 (NCT01377922)

After an initial open-label run-in phase, 38 patients were randomized in a double-blind fashion to either continue treatment with FIRDAPSE (n=16) or to a downward titration to placebo (n=22) over 7 days. Following the downward titration period, patients remained on blinded FIRDAPSE or placebo for 7 more days. Efficacy was assessed at Day 14 of the double-blind period. Patients were allowed to use stable dosages of peripherally acting cholinesterase inhibitors or oral immunosuppressants. Twenty-six percent of patients randomized to FIRDAPSE were receiving cholinesterase inhibitors, versus 36% in the placebo group, and 28% of patients randomized to FIRDAPSE were receiving oral immunosuppressant therapies, versus 34% in the placebo group.

Patients had a median age of 54 years (range: 21 to 88 years), 61% were female, and 90% were White. Eighty-four percent of patients had a diagnosis of autoimmune LEMS, and 16% of patients had a diagnosis of paraneoplastic LEMS.

During the double-blind period (from Baseline to Day 14), the QMG scores tended to worsen in both treatment groups, but there was significantly greater worsening in the placebo group than in the FIRDAPSE group (p=0.045). Similarly, the SGI score tended to worsen in both treatment groups during the double-blind period, but there was significantly greater worsening in the placebo group than in the FIRDAPSE group (p=0.003), as summarized in Table 3. These results indicate that in Study 1, patients randomized to placebo had a significantly greater worsening of muscle weakness and of global impression of the effects of the study treatment on their physical well-being, compared to patients who continued FIRDAPSE in the double-blind period.

Table 3. Change from Baseline to Day 14 in QMG Score and SGI Score in Study 1
Assessment | FIRDAPSE (n=16) | Placebo (n=21)
Primary Endpoints
QMG Scorea
Baseline (mean) | 6.4 | 5.6
Change from Baseline (Least Square Mean) | 0.4 | 2.2
FIRDAPSE-placebo Treatment Difference (Least Square Mean (95% CI)) | –1.7 (–3.4, –0.0)
p-valuec | 0.045
SGI Scoreb
Baseline (mean) | 5.6 | 5.9
Change from Baseline (Least Square Mean) | -0.8 | -2.6
FIRDAPSE-placebo Treatment Difference, (Least Square Mean (95% CI)) | 1.8 (0.7, 3.0)
p-valuec | 0.003
a. QMG Score range 0 (no impairment) to 39 (worst impairment)
b. SGI Score range 0 (least perceived benefit) to 7 (most perceived benefit)
c. Pairwise contrast at Day 14 from mixed-effects model with repeated measures.

The CGI-I score was significantly greater for patients randomized to placebo than for patients who continued treatment with FIRDAPSE, with a mean difference between FIRDAPSE and placebo of -1.1 (p=0.02), indicating that clinicians perceived a greater worsening of clinical symptoms in patients who were randomized to placebo and discontinued from FIRDAPSE treatment, compared to patients who continued FIRDAPSE in the double-blind period.

Study 2 (NCT02970162)

Patients on stable treatment with FIRDAPSE were randomized 1:1 in a double-blind fashion to either continue treatment with FIRDAPSE (n=13) or change to placebo (n=13) for 4 days. Efficacy was assessed at the end of the 4-day double-blind discontinuation period. Patients were allowed to use stable doses of peripherally acting cholinesterase inhibitors or corticosteroids. Sixty-one percent of patients randomized to FIRDAPSE were receiving cholinesterase inhibitors, versus 54% of patients randomized to placebo.

Corticosteroid use was similar between FIRDAPSE and placebo (8%). Patients with recent use of immunomodulatory therapies (e.g., azathioprine, mycophenolate, cyclosporine), rituximab, intravenous immunoglobulin G, and plasmapheresis were excluded from the study. Patients had a median age of 55.5 years (range: 31 to 75 years), 62% were female, and 88% were white.

From Baseline to Day 4, there was significantly greater worsening in the QMG score in the placebo group than in the FIRDAPSE group (p=0.0004), and also significantly greater worsening in the SGI score in the placebo group than in the FIRDAPSE group (p=0.0003), as summarized in Table 4. These results indicate that in Study 2, patients randomized to placebo had a significantly greater worsening of muscle weakness and of global impression of the effects of the study treatment on their physical well-being, compared to patients who continued FIRDAPSE in the double-blind period.

Table 4. Change from Baseline to Day 4 in QMG Scores and SGI Scores in Study 2
Assessment | FIRDAPSE (n=13) | Placebo (n=13)
QMG Scoresa
Baseline, Mean | 7.8 | 8.5
Change from Baseline, Least Square Meanc | 0.00 | 6.54
FIRDAPSE-placebo Treatment Difference, Least Square Mean (95% CI) | -6.54 (-9.78, -3.29)
p-valued | 0.0004
SGI Scoresb
Baseline, Mean | 6.1 | 5.8
Change from Baseline, Least Square Meanc | -0.64 | -3.59
FIRDAPSE-placebo Treatment Difference, Least Square Mean (95% CI) | 2.95 (1.53, 4.38)
p-valued | 0.0003
a. QMG Score range 0 (no impairment) to 39 (worst impairment)
b. SGI Score range 0 (least perceived benefit) to 7 (most perceived benefit)
c. Change from baseline for QMG total score was modeled as the response, with fixed effects terms for treatment and QMG at Baseline
d. p-value based on the Wilcoxon Rank Sum Test for treatment differences.

The clinical global impression improvement (CGI-I) score was significantly greater for patients randomized to placebo than for patients who continued treatment with FIRDAPSE, with a mean difference between FIRDAPSE and placebo of -2.7 (p=0.002), indicating that clinicians perceived a greater worsening of clinical symptoms in patients who were randomized to placebo and discontinued from FIRDAPSE treatment, compared to patients who continued FIRDAPSE in the double-blind period.

16 HOW SUPPLIED/STORAGE AND HANDLING

16.1 How Supplied

FIRDAPSE 10 mg tablets are white to off white-round, and functionally scored. Each tablet is debossed on the non-scored side with “CATALYST” and on the scored side with “211” above the score and “10” below the score. Tablets can be divided in half at the score. FIRDAPSE is supplied as follows:

Child Resistant Blister Pack

- Blister pack containing 10 tablets | NDC 69616-211-04
- Carton containing 12 blister packs (120 tablets total) | NDC 69616-211-06

Bottles

- 60 tablets | NDC 69616-211-08
- 240 tablets | NDC 69616-211-03

16.2 Storage and Handling

Store FIRDAPSE tablets at 20°C to 25°C (68°F to 77°F) with excursions permitted from 15°C to 30°C (59°F to 86°F) [see USP controlled room temperature]. See Dosage and Administration (2.5) for storage instructions for FIRDAPSE prepared suspension.

17 PATIENT COUNSELING INFORMATION

Advise the patient and/or caregiver to read the FDA-approved patient labeling (Medication Guide and Instructions for Use).

Risk of Seizures

Inform patients that FIRDAPSE can cause seizures, and to notify their healthcare provider if they experience a seizure [see Warnings and Precautions (5.1)].

Hypersensitivity

Instruct patients to inform their healthcare provider if they have signs or symptoms of hypersensitivity, and to seek emergency help if symptoms of anaphylaxis occur [see Warnings and Precautions (5.2)].

FIRDAPSE Dosing

Instruct patients to take FIRDAPSE exactly as prescribed. Patients should carefully follow the dose escalation schedule provided by their healthcare provider to safely achieve the therapeutic dosage [see Dosage and Administration (2)]. Inform patients that the tablets may be divided in half at the score, if needed. Instruct patients not to take a double dose to make up for a missed dose.

If they require a dosage in less than 5 mg increments, have difficulty swallowing tablets, or require feeding tubes, refer patients and/or caregivers to the Instructions for Use on how to prepare a 1 mg/mL suspension [see Dosage and Administration (2.5)]. If the patient requires treatment with the 1 mg/mL FIRDAPSE suspension, advise patients and/or caregivers that supplies required to prepare the suspension may be obtained at their local pharmacy.

Drug Interactions

Instruct patients to notify their healthcare provider prior to starting any new medication, including over-the-counter drugs [see Drug Interactions (7)].

Pregnancy

Instruct patients that if they are pregnant or plan to become pregnant while taking FIRDAPSE they should inform their healthcare provider. Advise patients that there is a pregnancy registry that monitors pregnancy outcomes in women exposed to FIRDAPSE during pregnancy and encourage them to enroll if they become pregnant while taking FIRDAPSE [see Use in Specific Populations (8.1)].

Storage

Advise patients to store FIRDAPSE at 68ºF to 77ºF (20ºC to 25ºC).

Instruct patients and/or caregivers who prepare the 1 mg/mL suspension of FIRDAPSE that it should be prepared daily and refrigerated between doses. The suspension can be stored under refrigeration for up to 24 hours. Instruct the patient and/or caregiver to discard any unused portion of the suspension after 24 hours.

Distributed by Catalyst Pharmaceuticals, Inc., Coral Gables, FL 33134
FIRDAPSE is a trademark of SERB S.A.
Catalyst and the Catalyst logo are trademarks of Catalyst Pharmaceuticals, Inc.

© 2024 Catalyst Pharmaceuticals, Inc. – All rights reserved.

MEDICATION GUIDE
FIRDAPSE® (FIR-dapse)
(amifampridine)
tablets, for oral use

Read this Medication Guide before you start taking FIRDAPSE and each time you get a refill. There may be new information. This information does not take the place of talking with your doctor about your medical condition or your treatment.

What is the most important information I should know about FIRDAPSE?
FIRDAPSE can cause seizures.

- You could have a seizure even if you never had a seizure before.
- Do not take FIRDAPSE if you have ever had a seizure.

Stop taking FIRDAPSE and call your doctor right away if you have a seizure while taking FIRDAPSE.

What is FIRDAPSE?
FIRDAPSE is a prescription medicine used to treat Lambert-Eaton myasthenic syndrome (LEMS) in people 6 years of
age and older.
It is not known if FIRDAPSE is safe or effective in children less than 6 years of age.

Do not take FIRDAPSE if you:

- have ever had a seizure.
- are allergic to amifampridine phosphate, or another aminopyridine.

Before you take FIRDAPSE, tell your doctor about all of your medical conditions. including if you:

- are taking another aminopyridine, such as compounded 3,4-diaminopyridine (3,4-DAP)
- have had a seizure
- have kidney problems
- have liver problems
- are pregnant or plan to become pregnant. It is not known if FIRDAPSE will harm your unborn baby. You and your doctor will decide if you should take FIRDAPSE while you are pregnant.
- There is a registry for women who become pregnant during treatment with FIRDAPSE. The purpose of this registry is to collect information about your health and your baby's health. Contact the registry as soon as you learn that you are pregnant, or ask your doctor to contact for you by calling 855-212-5856 (toll free), contacting the Fax number 877-867-1874 (toll free), emailing the Pregnancy Coordinating Center at firdapsepregnancyregistry@ubc.com, or visiting the study website www.firdapsepregnancystudy.com
- are breastfeeding or plan to breastfeed. It is not known if FIRDAPSE passes into your breast milk. Talk to your doctor about the best way to feed your baby while taking FIRDAPSE.

Tell your doctor about all the medicines you take, including prescription and over-the-counter medicines, vitamins and herbal supplements.

How should I take FIRDAPSE?

- If your dose is less than 5mg, you have trouble swallowing tablets, or a feeding tube is needed, see the detailed Instructions for Use on how to take and prepare a suspension of FIRDAPSE.
- Take FIRDAPSE exactly as your doctor tells you to take it.
- Do not change your dose of FIRDAPSE.
- Do not stop taking FIRDAPSE without first talking to your doctor.
- FIRDAPSE tablets are scored and can be split if less than a full tablet is needed for you to get the right dose.
- FIRDAPSE can be taken with or without food.
- If you miss a dose of FIRDAPSE, skip that dose and take your next dose at your next scheduled dose time. Do not double your dose to make up the missed dose.
- Do not take FIRDAPSE together with other medicines known to increase the risk of seizures.
- If you take too much FIRDAPSE, call your doctor or go to the nearest hospital emergency room right away.

What are the possible side effects of FIRDAPSE?
FIRDAPSE may cause serious side effects, including:

- Seizures. See “What is the most important information I should know about FIRDAPSE?”
- Serious allergic reactions, such as anaphylaxis. FIRDAPSE can cause serious allergic reactions. Stop taking FIRDAPSE and call your doctor right away or get emergency medical help if you have:
  - shortness of breath or trouble breathing
  - swelling of your throat or tongue
  - hives

The most common side effects of FIRDAPSE include:

- tingling around the mouth, tongue, face, fingers, toes, and other body parts
- upper respiratory infection
- stomach pain
- nausea
- diarrhea
- headache
- increased liver enzymes
- back pain
- high blood pressure
- muscle spasms

Tell your doctor if you have any side effect that bothers you or that does not go away. These are not all the possible side effects of FIRDAPSE.
Call your doctor for medical advice about side effects. You may report side effects to FDA at 1-800-FDA-1088.

How should I store FIRDAPSE?

- Store FIRDAPSE tablets at room temperature between 68ºF to 77ºF (20ºC to 25ºC).
- Safely throw away FIRDAPSE tablets that are out of date or no longer needed.
- Store FIRDAPSE prepared oral suspension in the refrigerator between 36°F to 46°F (2°C to 8°C) between doses for up to 24 hours.
- Safely throw away unused FIRDAPSE oral suspension after 24 hours.

Keep FIRDAPSE and all medicines out of the reach of children.

General Information about the safe and effective use of FIRDAPSE
Medicines are sometimes prescribed for purposes other than those listed in a Medication Guide. Do not use FIRDAPSE for a condition for which it was not prescribed. Do not give FIRDAPSE to other people, even if they have the same symptoms that you have. It may harm them.
If you would like more information, talk to your doctor or pharmacist. You can ask your pharmacist or doctor for information about FIRDAPSE that is written for health professionals.

What are the ingredients in FIRDAPSE?
Active ingredient: amifampridine
Inactive ingredients: calcium stearate, colloidal silicon dioxide, and microcrystalline cellulose.
Distributed by Catalyst Pharmaceuticals, Inc., Coral Gables, FL 33134
For more information, go to www.YourCatalystPathways.com or call 1-833-422-8259

This Medication Guide has been approved by the U.S. Food and Drug Administration

Revised: 5/2024

Instructions for Use

FIRDAPSE (FIR-dapse)

(amifampridine) tablets

for oral use

This Instructions for Use contains information on how to mix and use FIRDAPSE prepared suspension. The FIRDAPSE prepared suspension can be used for people who are prescribed a dosage that cannot be obtained with whole or half tablets, who have trouble swallowing tablets, or who have a feeding tube.

Prepare FIRDAPSE oral suspension each day.

Supplies you will need:

You can get these supplies at your local pharmacy.

your FIRDAPSE tablets

empty bottle with cap (50-100 mL recommended)

sterile water

oral syringe with catheter tip (10mL, may require smaller syringe for dosing)

Instructions to make a 1 mg/mL suspension:

Important:

- Do not use any foods or liquids other than sterile water to mix FIRDAPSE.
- You can prepare each dose separately or all of your doses for the day at one time.

Step 1

Step 2

Step 3

Place the number of FIRDAPSE tablets you need for your dose or doses in a bottle.

For each tablet, add 10 mL of water to the bottle. Measure the water with an oral syringe, and inject the water into the bottle.
Note: Depending on the number of tablets and the size of the syringe, you may need to measure and inject the water more than one time.

Secure the cap back on the bottle. Wait for 5 minutes. Shake well for 30 seconds.

Instructions to administer the prepared suspension:

Important:

- Prepare fresh suspensions daily.
- If you prepare all of your doses for the day at one time, refrigerate the suspension between doses. Shake well before drawing up each dose.

OPTION 1 To administer by mouth:

Step 4

Step 5

Remove the bottle cap and use an oral syringe with a catheter tip to measure the prescribed dose.

Push syringe plunger to administer by mouth.
Note: Depending on the dose and size of syringe, you may need to repeat steps 4 and 5 until the prescribed dose is given.

OPTION 2 To administer by feeding tube:

Important:

- Do not use any foods or liquids other than sterile water to mix FIRDAPSE.
- Use only an oral syringe with a catheter tip to give FIRDAPSE through the feeding tube. Talk to your healthcare provider about the size catheter tipped syringe you should use.

Step 4

Step 5

Remove the bottle cap and use an oral syringe with a catheter tip to measure the prescribed dose.

Inject the medicine using the oral syringe with a catheter tip into the feeding tube right away.
Note: Depending on the dose and size of syringe, you may need to repeat steps 4 and 5 until the prescribed dose is given.

Step 6

Step 7

To flush the feeding tube: Refill the syringe with 10 mL of sterile water.

Shake the syringe, insert the catheter tip into the feeding tube to flush any remaining medicine from the feeding tube into the stomach.

How should I store FIRDAPSE?

Firdapse tablets:

- Store FIRDAPSE tablets at room temperature between 68ºF to 77ºF (20ºC to 25ºC).
- Safely throw away FIRDAPSE tablets that are out of date or no longer needed.

Firdapse prepared suspension:

- Store FIRDAPSE prepared oral suspension in the refrigerator between 36°F to 46°F (2°C to 8°C) between doses for up to 24 hours.
- Safely throw away unused FIRDAPSE oral suspension after 24 hours.

Distributed by Catalyst Pharmaceuticals, Inc., Coral Gables, FL 33134

For more information, go to www.YourCatalystPathways.com or call 1-833-422-8259

This Instructions for Use has been approved by the U.S. Food and Drug Administration. Approved: 5/2024

PRINCIPAL DISPLAY PANEL - 10 mg Tablet Blister Pack Carton

Rx Only
NDC 69616-211-06

120 Tablets Total
Provided in 12 Child-Resistant Blister Cards
Of 10 Tablets Each

FIRDAPSE®
(amifampridine) Tablets
10 mg per Tablet

Manufactured for:
Catalyst Pharmaceuticals, Inc.
Coral Gables, FL 33134